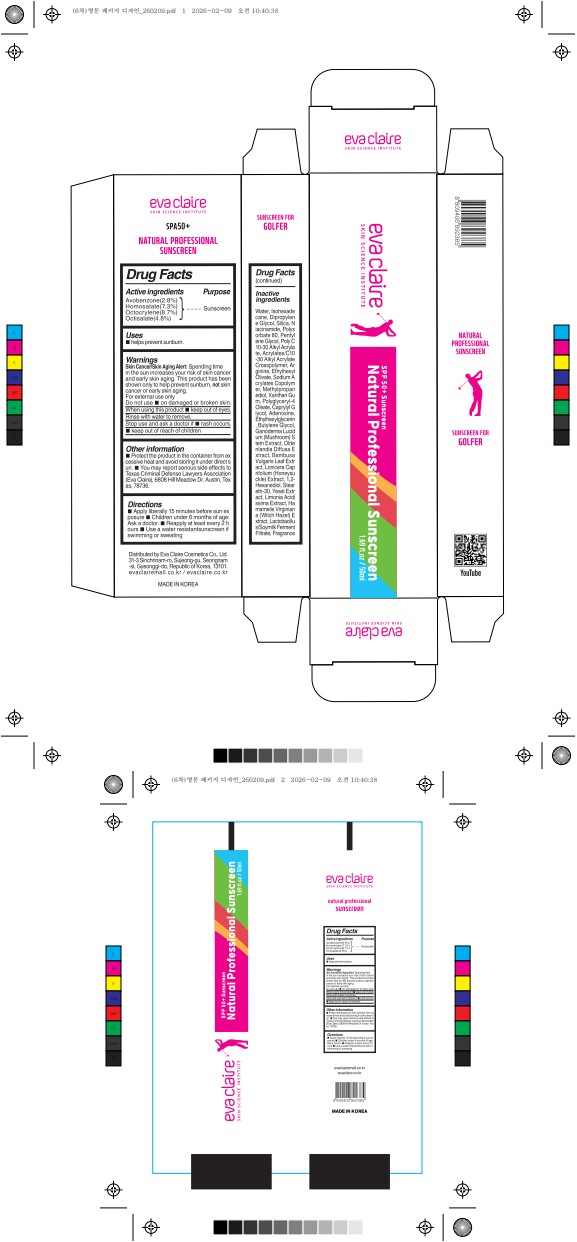 DRUG LABEL: Eva Claire Natural Professional Sunscreen
NDC: 87364-100 | Form: CREAM
Manufacturer: Eva Claire Cosmetics Co., Ltd.
Category: otc | Type: HUMAN OTC DRUG LABEL
Date: 20260211

ACTIVE INGREDIENTS: OCTOCRYLENE 4.35 g/50 mL; HOMOSALATE 3.65 g/50 mL; AVOBENZONE 0.7 g/50 mL; OCTISALATE 2.4 g/50 mL
INACTIVE INGREDIENTS: SILICA; NIACINAMIDE; ARGININE; ADENOSINE; CAPRYLYL GLYCOL; HAMAMELIS VIRGINIANA (WITCH HAZEL) LEAF WATER; BAMBUSA VULGARIS LEAF; BUTYLENE GLYCOL; SCLEROMITRION DIFFUSUM; LIMONIA ACIDISSIMA WOOD; POLYGLYCERYL-4 OLEATE; ACRYLATES/C10-30 ALKYL ACRYLATE CROSSPOLYMER (60000 MPA.S); ISOHEXADECANE; DIPROPYLENE GLYCOL; STEARYL ACRYLATE POLYMER (110000 MW); XANTHAN GUM; METHYLPROPANEDIOL; GANODERMA LUCIDUM STEM; 1,2-HEXANEDIOL; YEAST; ETHYLHEXYLGLYCERIN; LONICERA CAPRIFOLIUM FLOWER; STEARETH-30; POLYSORBATE 80; PENTYLENE GLYCOL; ETHYLHEXYL OLIVATE; WATER

87364-100 Eva Claire Natural Professional Sunscreen

ACTIVE INGREDIENT

Avobenzone 2.8%
Homosalate 7.3%
Octocrylene 8.7%

Octisalate 4.8%

PURPOSE

Sunscreen

INDICATIONS AND USAGE

■ Helps prevent sunburn.

WARNINGS

Skin Cancer/Skin Aging Alert: Spending time in the sun increases your risk of skin cancer and early skin aging. This porduct has been shown only to help prevent sunburn, not skin cancer or early skin aging.
For external use only

DO NOT USE

■ on damaged skin or broken skin

WHEN USING

■ keep out of eyes. Rinse with water to remove.

stop use and ask a doctor if ■ rash occurs.

KEEP OUT OF REACH OF CHILDREN

If swallowed, get medical help or contact poison control center right away

INACTIVE INGREDIENT

Water
Isohexadecane
Dipropylene Glycol
Silica
Niacinamide
Polysorbate 80
Pentylene Glycol
Poly C10-30 Alkyl Acrylate
Acrylates/C10-30 Alkyl Acrylate Crosspolymer
Arginine
Ethylhexyl Olivate
Sodium Acrylates Copolymer
Methylpropanediol
Xanthan Gum
Polyglyceryl-4 Oleate
Caprylyl Glycol
Adenosine
Ethylhexylglycerin
Butylene Glycol
Ganoderma Lucidum (Mushroom) Stem Extract
Oldenlandia Diffusa Extract
Bambusa Vulgaris Leaf Extract
Lonicera Caprifolium (Honeysuckle) Extract
1,2-Hexanediol
Steareth-30
Yeast Extract
Limonia Acidissima Extract
Hamamelis Virginiana (Witch Hazel) Extract
Lactobacillus/Soymilk Ferment Filtrate
Fragrance

DOSAGE AND ADMINISTRATION

■ Apply liberally 15 minutes before sun exposure.
■ Children under 6 months of age: Ask a doctor.

■ Reapply at least every 2 hours.

■ Use a water-resistant sunscreen if swimming or sweating

OTHER SAFETY INFORMATION

■ Protect the product in the container from excessive heat and avoid storing it under direct sun.

■ You may report serious side effects to Texas Criminal Defense Lawyers Association(Eva Claire), 6808 Hill Meadow Dr. Austin, Texas, 78736.